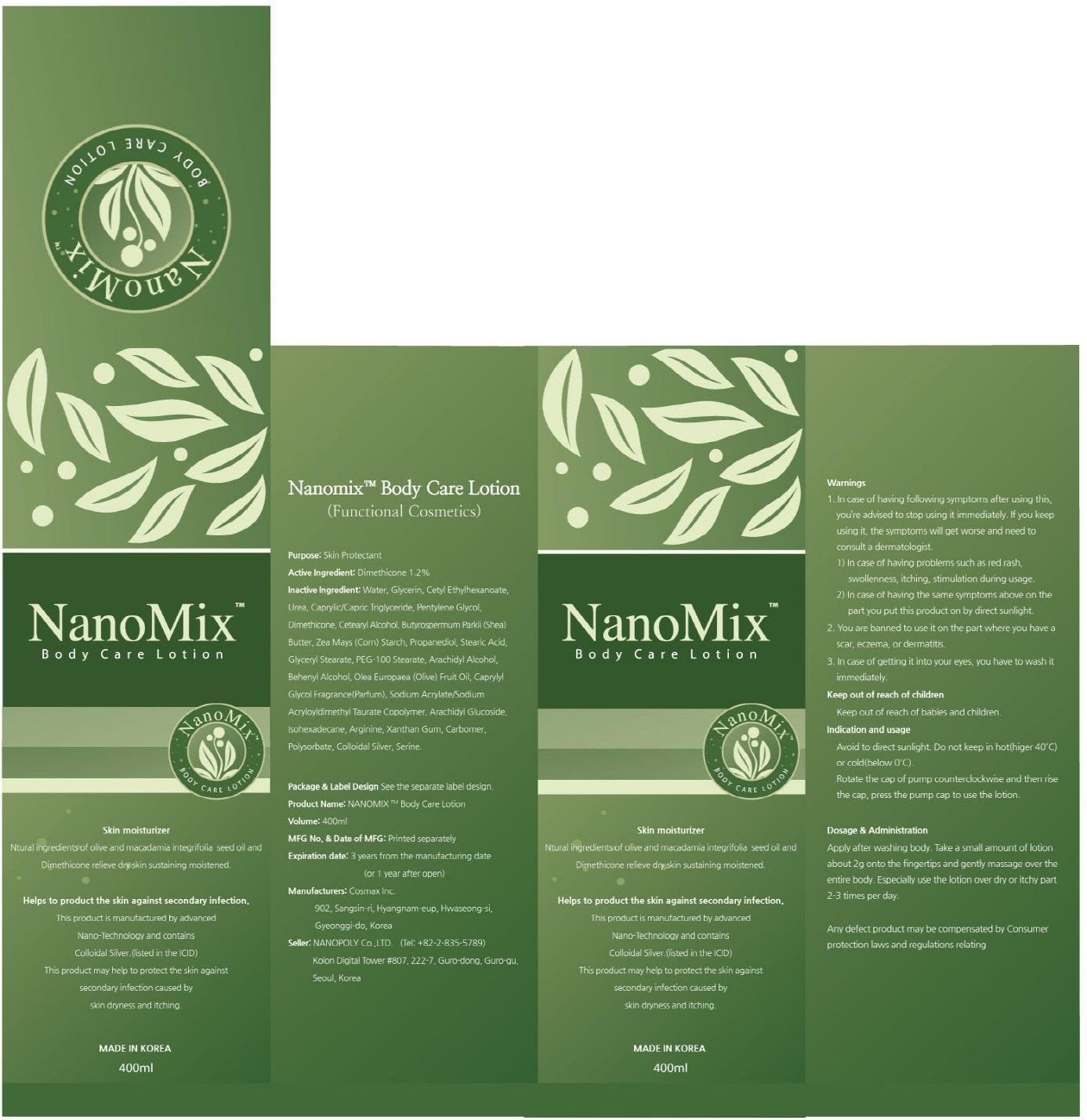 DRUG LABEL: NANOMIX BODY CARE
NDC: 54170-110 | Form: LOTION
Manufacturer: NANOPOLY CO., LTD.
Category: otc | Type: HUMAN OTC DRUG LABEL
Date: 20130819

ACTIVE INGREDIENTS: Dimethicone 4.8 mg/400 mL
INACTIVE INGREDIENTS: Water; Glycerin

ACTIVE INGREDIENT

Active Ingredient: Dimethicone 1.2%

INACTIVE INGREDIENT

Inactive Ingredient: Water, Glycerin, Cetyl Ethylhexanoate, Urea, Caprylic/Capric Triglyceride, Pentylene Glycol , Dimethicone, Cetearyl Alcohol, Butyrospermum Parkii (Shea) Butter, Zea Mays (Corn) Starch, Propanediol, Stearic Acid, Glyceryl Stearate, PEG-100 Stearate, Arachidyl Alcohol, Behenyl Alcohol, Olea Europaea (Olive) Fruit Oil, Caprylyl Glycol Fragrance(Parfum), Sodium Acrylate/Sodium Acryloyldimethyl Taurate Copolymer, Arachidyl Glucoside, Isohexadecane, Arginine, Xanthan Gum, Carbomer, Polysorbate, Colloidal Silver, Serine

PURPOSE

Purpose: Skin Protectant

WARNINGS

1. In case of having following symptoms after using this, you’re advised to stop using it immediately. If you keep using it, the symptoms will get worse and need to consult a dermatologist.
1) In case of having problems such as red rash, swollenness, itching, stimulation during usage.
2) In case of having the same symptoms above on the part you put this product on by direct sunlight.
2. You are banned to use it on the part where you have a scar, eczema, or dermatitis.
3. In case of getting it into your eyes, you have to wash it immediately.

KEEP OUT OF REACH OF CHILDREN

Keep out of reach of babies and children.

INDICATIONS AND USAGE

Indication and usage:
Avoid to direct sunlight.
Do not keep in hot(higer 40C) or cold(below 0C).
Rotate the cap of pump counterclockwise and then rise the cap, press the pump cap to use the lotion.

DOSAGE AND ADMINISTRATION

Apply after washing body.
Take a small amount of lotion about 2g onto the fingertips and gently massage over the entire body.
Especially use the lotion over dry or itchy part 2-3 times per day.